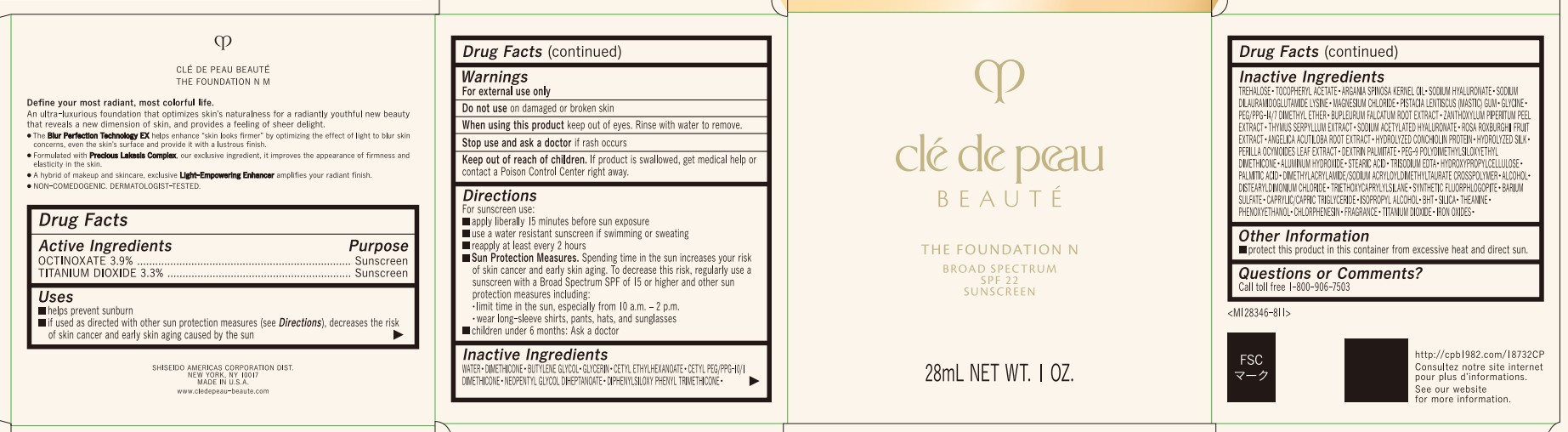 DRUG LABEL: cle de peau BEAUTE THE FOUNDATION N M
NDC: 58411-012 | Form: PASTE
Manufacturer: Shiseido Americas Corporation
Category: otc | Type: HUMAN OTC DRUG LABEL
Date: 20260224

ACTIVE INGREDIENTS: OCTINOXATE 1.165 g/28 mL; TITANIUM DIOXIDE 0.986 g/28 mL
INACTIVE INGREDIENTS: GLYCERIN; CETYL ETHYLHEXANOATE; CETYL PEG/PPG-10/1 DIMETHICONE (HLB 2); NEOPENTYL GLYCOL DIHEPTANOATE; DIPHENYLSILOXY PHENYL TRIMETHICONE; TREHALOSE; DIMETHICONE; .ALPHA.-TOCOPHEROL ACETATE; ARGANIA SPINOSA KERNEL OIL; WATER; SODIUM HYALURONATE; SODIUM DILAURAMIDOGLUTAMIDE LYSINE; MAGNESIUM CHLORIDE; PISTACIA LENTISCUS (MASTIC) GUM; GLYCINE; PEG/PPG-14/7 DIMETHYL ETHER; BUTYLENE GLYCOL; BUPLEURUM FALCATUM ROOT; ZANTHOXYLUM PIPERITUM FRUIT RIND; THYMUS SERPYLLUM; SODIUM ACETYLATED HYALURONATE; ROSA ROXBURGHII FRUIT; ANGELICA ACUTILOBA ROOT; PERILLA OCYMOIDES SEED OIL; DEXTRIN PALMITATE (CORN; 20000 MW); PEG-9 POLYDIMETHYLSILOXYETHYL DIMETHICONE; ALUMINUM HYDROXIDE; STEARIC ACID; TRISODIUM EDTA; HYDROXYPROPYLCELLULOSE; PALMITIC ACID; ALCOHOL; DISTEARYLDIMONIUM CHLORIDE; TRIETHOXYCAPRYLYLSILANE; MAGNESIUM POTASSIUM ALUMINOSILICATE FLUORIDE; BARIUM SULFATE; CAPRYLIC/CAPRIC TRIGLYCERIDE; BUTYLATED HYDROXYTOLUENE; SILICA; THEANINE; PHENOXYETHANOL; CHLORPHENESIN; FERRIC OXIDE RED

cle de peau BEAUTE THE FOUNDATION N M

Drug Facts

Active Ingredients | Purpose
Octinoxate 3.9% | Sunscreen
Titanium Dioxide 3.3% | Sunscreen

Uses

- helps prevent sunburn
- if used as directed with other sun protection measures (see Directions), decreases the risk of skin cancer and early skin aging caused by the sun

Warnings

For external use only

Do not use on damaged or broken skin

When using this product keep out of eyes. Rinse with water to remove.

Stop use and ask a doctor if rash occurs

Keep out of reach of children. If product is swallowed, get medical help or contact a Poison Control Center right away.

Directions

For sunscreen use:

- apply liberally 15 minutes before sun exposure
- use a water resistant sunscreen if swimming or sweating
- reapply at least every 2 hours
- Sun Protection Measures. Spending time in the sun increases your risk of skin cancer and early skin aging. To decrease this risk, regularly use a sunscreen with a Broad Spectrum SPF of 15 or higher and other sun protection measures including:

• limit time in the sun, especially from 10 a.m. - 2 p.m.

• wear long-sleeve shirts, pants, hats, and sunglasses

- children under 6 months: Ask a doctor

INACTIVE INGREDIENT

WATER･DIMETHICONE･BUTYLENE GLYCOL･GLYCERIN･CETYL ETHYLHEXANOATE･CETYL PEG/PPG-10/1 DIMETHICONE･NEOPENTYL GLYCOL DIHEPTANOATE･DIPHENYLSILOXY PHENYL TRIMETHICONE･TREHALOSE･TOCOPHERYL ACETATE･ARGANIA SPINOSA KERNEL OIL･SODIUM HYALURONATE･SODIUM DILAURAMIDOGLUTAMIDE LYSINE･MAGNESIUM CHLORIDE･PISTACIA LENTISCUS (MASTIC) GUM･GLYCINE･PEG/PPG-14/7 DIMETHYL ETHER･BUPLEURUM FALCATUM ROOT EXTRACT･ZANTHOXYLUM PIPERITUM PEEL EXTRACT･THYMUS SERPYLLUM EXTRACT･SODIUM ACETYLATED HYALURONATE･ROSA ROXBURGHII FRUIT EXTRACT･ANGELICA ACUTILOBA ROOT EXTRACT･HYDROLYZED CONCHIOLIN PROTEIN･HYDROLYZED SILK･PERILLA OCYMOIDES LEAF EXTRACT･DEXTRIN PALMITATE･PEG-9 POLYDIMETHYLSILOXYETHYL DIMETHICONE･ALUMINUM HYDROXIDE･STEARIC ACID･TRISODIUM EDTA･HYDROXYPROPYLCELLULOSE･PALMITIC ACID･DIMETHYLACRYLAMIDE/SODIUM ACRYLOYLDIMETHYLTAURATE CROSSPOLYMER･ALCOHOL･DISTEARYLDIMONIUM CHLORIDE･TRIETHOXYCAPRYLYLSILANE･SYNTHETIC FLUORPHLOGOPITE･BARIUM SULFATE･CAPRYLIC/CAPRIC TRIGLYCERIDE･ISOPROPYL ALCOHOL･BHT･SILICA･THEANINE･PHENOXYETHANOL･CHLORPHENESIN･FRAGRANCE･TITANIUM DIOXIDE･IRON OXIDES･

Other Information

- protect this product in this container from excessive heat and direct sunlight

Questions or Comments?

Call toll free 1-800-906-7503

PRINCIPAL DISPLAY PANEL - 28 mL Jar Carton - O50

clé de peau

BEAUTÉ

THE FOUNDATION N

BROAD SPECTRUM

SPF 22

SUNSCREEN

28mL NET WT. 1 OZ.

PRINCIPAL DISPLAY PANEL - 28 mL Jar Carton - I10

clé de peau

BEAUTÉ

THE FOUNDATION N

BROAD SPECTRUM

SPF 22

SUNSCREEN

28mL NET WT. 1 OZ.

PRINCIPAL DISPLAY PANEL - 28 mL Jar Carton - O10

clé de peau

BEAUTÉ

THE FOUNDATION N

BROAD SPECTRUM

SPF 22

SUNSCREEN

28mL NET WT. 1 OZ.

PRINCIPAL DISPLAY PANEL - 28 mL Jar Carton - O20

clé de peau

BEAUTÉ

THE FOUNDATION N

BROAD SPECTRUM

SPF 22

SUNSCREEN

28mL NET WT. 1 OZ.

PRINCIPAL DISPLAY PANEL - 28 mL Jar Carton - O30

clé de peau

BEAUTÉ

THE FOUNDATION N

BROAD SPECTRUM

SPF 22

SUNSCREEN

28mL NET WT. 1 OZ.

PRINCIPAL DISPLAY PANEL - 28 mL Jar Carton - O40

clé de peau

BEAUTÉ

THE FOUNDATION N

BROAD SPECTRUM

SPF 22

SUNSCREEN

28mL NET WT. 1 OZ.

PRINCIPAL DISPLAY PANEL - 28 mL Jar Carton - O60

clé de peau

BEAUTÉ

THE FOUNDATION N

BROAD SPECTRUM

SPF 22

SUNSCREEN

28mL NET WT. 1 OZ.

PRINCIPAL DISPLAY PANEL - 28 mL Jar Carton - O80

clé de peau

BEAUTÉ

THE FOUNDATION N

BROAD SPECTRUM

SPF 22

SUNSCREEN

28mL NET WT. 1 OZ.

PRINCIPAL DISPLAY PANEL - 28 mL Jar Carton - O100

clé de peau

BEAUTÉ

THE FOUNDATION N

BROAD SPECTRUM

SPF 22

SUNSCREEN

28mL NET WT. 1 OZ.

PRINCIPAL DISPLAY PANEL - 28 mL Jar Carton - B10

clé de peau

BEAUTÉ

THE FOUNDATION N

BROAD SPECTRUM

SPF 22

SUNSCREEN

28mL NET WT. 1 OZ.

PRINCIPAL DISPLAY PANEL - 28 mL Jar Carton - B20

clé de peau

BEAUTÉ

THE FOUNDATION N

BROAD SPECTRUM

SPF 22

SUNSCREEN

28mL NET WT. 1 OZ.

PRINCIPAL DISPLAY PANEL - 28 mL Jar Carton - B30

clé de peau

BEAUTÉ

THE FOUNDATION N

BROAD SPECTRUM

SPF 22

SUNSCREEN

28mL NET WT. 1 OZ.

PRINCIPAL DISPLAY PANEL - 28 mL Jar Carton - B40

clé de peau

BEAUTÉ

THE FOUNDATION N

BROAD SPECTRUM

SPF 22

SUNSCREEN

28mL NET WT. 1 OZ.

PRINCIPAL DISPLAY PANEL - 28 mL Jar Carton - B50

clé de peau

BEAUTÉ

THE FOUNDATION N

BROAD SPECTRUM

SPF 22

SUNSCREEN

28mL NET WT. 1 OZ.

PRINCIPAL DISPLAY PANEL - 28 mL Jar Carton - BF10

clé de peau

BEAUTÉ

THE FOUNDATION N

BROAD SPECTRUM

SPF 22

SUNSCREEN

28mL NET WT. 1 OZ.